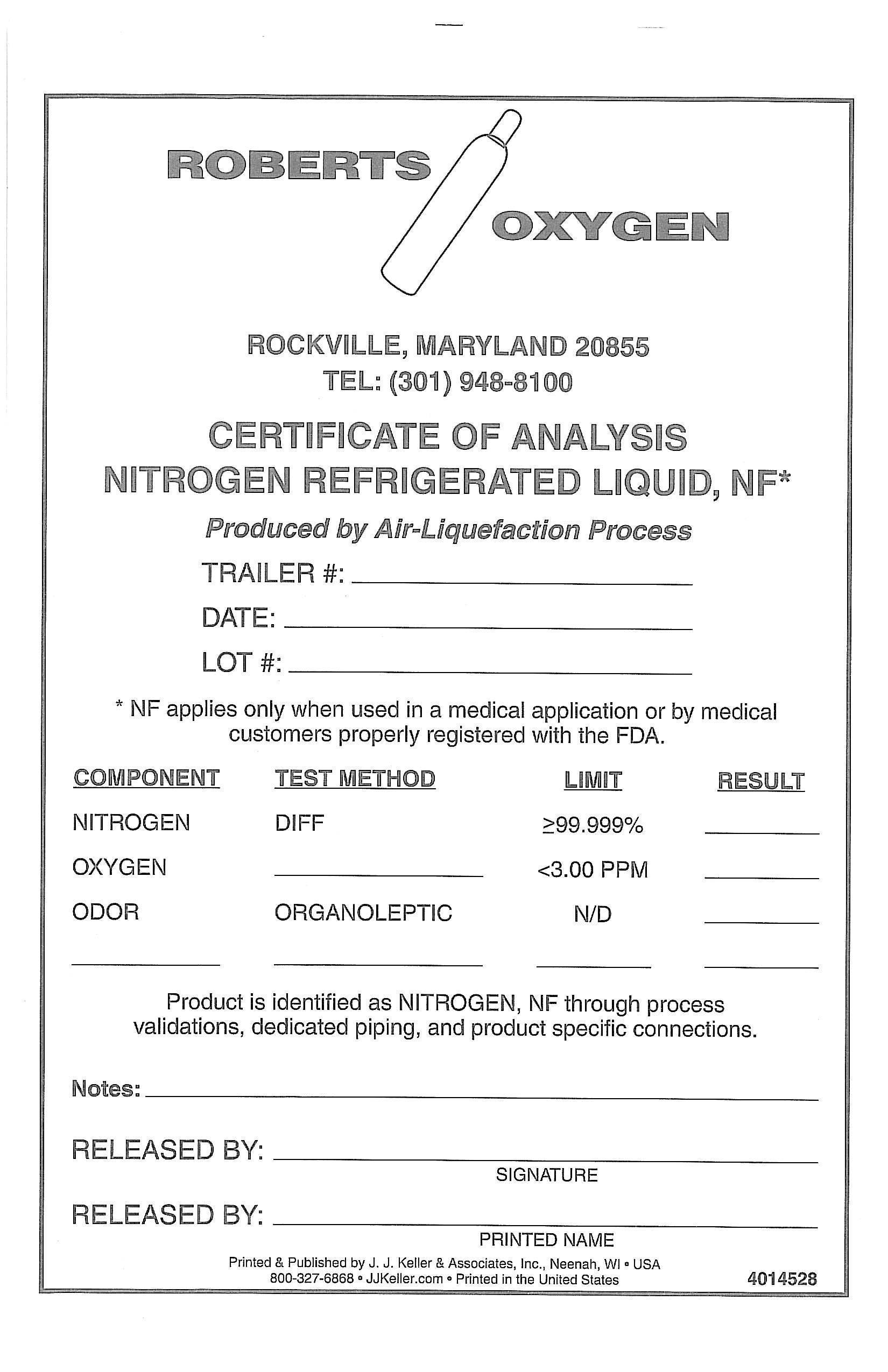 DRUG LABEL: Nitrogen
NDC: 46123-440 | Form: GAS
Manufacturer: Roberts Oxygen Company, Inc.
Category: prescription | Type: HUMAN PRESCRIPTION DRUG LABEL
Date: 20251117

ACTIVE INGREDIENTS: NITROGEN 990 mL/1 L

NITROGEN REFRIGERATED LIQUID, NF -440

PACKAGE LABEL

ROBERTS OXYGEN
ROCKVILLE, MARYLAND 20866
TEL: (301) 948-8100

CERTIFICATE OF ANALYSIS
NITROGEN REFRIGERATED LIQUID, NF*

PRODUCED BY AIR-LIQUEFACTION PROCESS

TRAILER#: ______________

DATE: _________________

LOT#: _________________

*NF applies only when used in a medical application or by medical customers properly registered with the FDA.

Component Test Method Limit Result

NITROGEN DIFF >99.999% _______

OXYGEN ________ <3.0 PPM _______

Odor ORGANOLEPTIC N/D ______

________ _________ _________ _________

Product is identified as NITROGEN, NF through process validations, dedicated piping, and product specific connections.

Notes: _____________________________________

RELEASED BY: ____________________________

SIGNATURE

RELEASED BY: ____________________________

PRINTED NAME

Printed & Published by J.J. KELLER & ASSPCIATES, INC., Neenah, WI * USP

(800) 327-6868 *jjkeller.com * Printer in the Unitied States